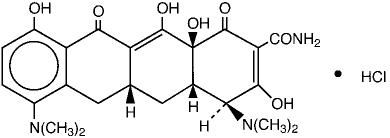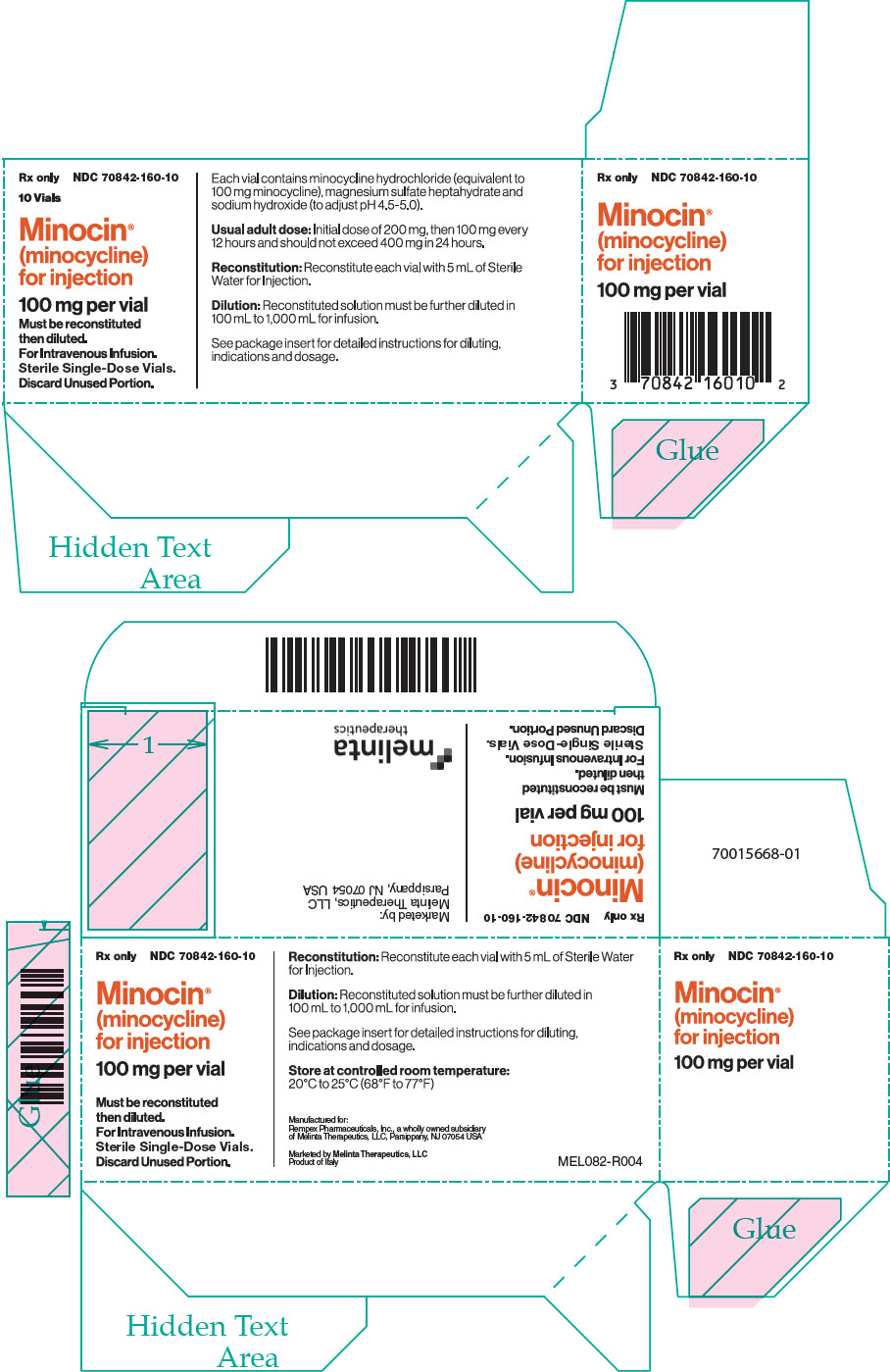 DRUG LABEL: Minocin
NDC: 70842-160 | Form: INJECTION
Manufacturer: Melinta Therapeutics, LLC
Category: prescription | Type: HUMAN PRESCRIPTION DRUG LABEL
Date: 20250911

ACTIVE INGREDIENTS: MINOCYCLINE HYDROCHLORIDE 100 mg/1 1
INACTIVE INGREDIENTS: MAGNESIUM SULFATE HEPTAHYDRATE 269 mg/1 1; SODIUM HYDROXIDE

MINOCIN®
Minocycline For Injection
100 Mg/Vial

Rx Only

To reduce the development of drug-resistant bacteria and maintain the effectiveness of MINOCIN® (minocycline) for Injection and other antibacterial drugs, MINOCIN® (minocycline) for injection should be used only to treat or prevent infections that are proven or strongly suspected to be caused by bacteria.

DESCRIPTION

MINOCIN (minocycline) for Injection, is a sterile formulation of a semisynthetic derivative of tetracycline. The chemical name of minocycline is 4,7-Bis(dimethylamino)- 1,4,4a,5,5a,6,11,12a-octahydro-3,10,12,12a- tetrahydroxy-1,11-dioxo-2- naphthacenecarboxamide monohydrochloride.

Its structural formula is:

C23H27N3O7∙HCl

M.W. 493.94

MINOCIN is supplied as a sterile yellow to amber lyophilized powder for intravenous infusion. Each vial contains minocycline HCl equivalent to 100 mg minocycline, 269 mg magnesium sulfate heptahydrate (2.2 mEq of magnesium) (an inactive ingredient) and sodium hydroxide (to adjust pH). When reconstituted with 5 mL of Sterile Water for Injection USP the pH ranges from 4.5 to 5.0.

CLINICAL PHARMACOLOGY

Following a single dose of Minocin 200 mg administered intravenously to 10 healthy male subjects, serum concentrations of minocycline ranged from 2.52 to 6.63 mcg/mL (average 4.18 mcg/mL) at the end of infusion and 0.82 to 2.64 mcg/mL (average 1.38 mcg/mL) after 12 hours. In a group of 5 healthy male subjects, serum concentrations of minocycline ranged from 1.4 to1.8 mcg/mL at the end of the dosing interval following administration of Minocin 100 mg every 12 hours for three days. When Minocin 200 mg once daily was administered for three days, serum concentrations of minocycline were approximately 1 mcg/mL at 24 hours. The serum elimination half-life of minocycline following administration of either Minocin 100 mg every 12 hours or 200 mg once daily was not significantly different and ranged from 15 to 23 hours. The serum elimination half-life of minocycline ranged from 11 to 16 hours in subjects with hepatic impairment (n=7) and 18 to 69 hours in subjects with renal impairment (n=5). In comparison, the serum elimination half-life of minocycline ranged from 11 to 17 hours following a single dose of oral minocycline 200 mg in healthy subjects (n=12).

Microbiology

Mechanism of Action

The tetracyclines are primarily bacteriostatic and are thought to exert their antimicrobial effect by the inhibition of protein synthesis. The tetracyclines, including minocycline, have a similar antimicrobial spectrum of activity against a wide range of Gram-positive and Gram-negative bacteria. Cross-resistance of these bacteria to tetracyclines is common.

List of Microorganisms

Minocycline has been shown to be active against most isolates of the following bacteria, both in vitro and in clinical infections as described in the INDICATIONS AND USAGE section:

Gram-positive Bacteria
Bacillus anthracis
Listeria monocytogenes
Staphylococcus aureus
Streptococcus pneumoniae

Gram-negative Bacteria
Bartonella bacilliformis
Brucella species
Klebsiella granulomatis
Campylobacter fetus
Francisella tularensis
Vibrio cholerae
Yersinia pestis
Acinetobacter species
Enterobacter aerogenes
Escherichia coli
Haemophilus influenzae
Klebsiella species
Neisseria meningitidis
Shigella species

Other Microorganisms
Actinomyces species
Borrelia recurrentis
Chlamydophila psittaci
Chlamydia trachomatis
Clostridium species
Entamoeba species
Fusobacterium nucleatum subspecies fusiforme
Mycobacterium marinum
Mycoplasma pneumoniae
Propionibacterium acnes
Rickettsiae
Treponema pallidum subspecies pallidum
Treponema pallidum subspecies pertenue
Ureaplasma urealyticum

Susceptibility Test Methods

For specific information regarding susceptibility test interpretive criteria and associated test methods and quality control standards recognized by FDA for this drug, please see: https://www.fda.gov/STIC.

INDICATIONS AND USAGE

MINOCIN® Intravenous is indicated in the treatment of the following infections due to susceptible isolates of the designated bacteria:

Rocky Mountain spotted fever, typhus fever and the typhus group, Q fever, rickettsialpox and tick fevers caused by rickettsiae.
Respiratory tract infections caused by Mycoplasma pneumoniae.
Lymphogranuloma venereum caused by Chlamydia trachomatis.
Psittacosis (Ornithosis) due to Chlamydophila psittaci.
Trachoma caused by Chlamydia trachomatis, although the infectious agent is not always eliminated, as judged by immunofluorescence.
Inclusion conjunctivitis caused by Chlamydia trachomatis.
Nongonococcal urethritis, endocervical, or rectal infections in adults caused by Ureaplasma urealyticum or Chlamydia trachomatis.
Relapsing fever due to Borrelia recurrentis.
Plague due to Yersinia pestis.
Tularemia due to Francisella tularensis.
Cholera caused by Vibrio cholerae.
Campylobacter fetus infections caused by Campylobacter fetus.
Brucellosis due to Brucella species (in conjunction with streptomycin).
Bartonellosis due to Bartonella bacilliformis.
Granuloma inguinale caused by Klebsiella granulomatis.

Minocycline is indicated for the treatment of infections caused by the following Gram-negative bacteria when bacteriologic testing indicates appropriate susceptibility to the drug:

Escherichia coli.
Enterobacter aerogenes.
Shigella species.
Acinetobacter species.
Respiratory tract infections caused by Haemophilus influenzae.
Respiratory tract and urinary tract infections caused by Klebsiella species.

MINOCIN® Intravenous is indicated for the treatment of infections caused by the following Gram-positive bacteria when bacteriologic testing indicates appropriate susceptibility to the drug:

Upper respiratory tract infections caused by Streptococcus pneumoniae.
Skin and skin structure infections caused by Staphylococcus aureus (Note: Minocycline is not the drug of choice in the treatment of any type of staphylococcal infection.)

When penicillin is contraindicated, minocycline is an alternative drug in the treatment of the following infections:

Meningitis due to Neisseria meningitidis.
Syphilis caused by Treponema pallidum subspecies pallidum.
Yaws caused by Treponema pallidum subspecies pertenue.
Listeriosis due to Listeria monocytogenes.
Anthrax due to Bacillus anthracis.
Vincent's infection caused by Fusobacterium fusiforme.
Actinomycosis caused by Actinomyces israelii.
Infections caused by Clostridium species.

In acute intestinal amebiasis, minocycline may be a useful adjunct to amebicides.

In severe acne, minocycline may be useful adjunctive therapy.

To reduce the development of drug-resistant bacteria and maintain the effectiveness of MINOCIN® (minocycline) for Injection and other antibacterial drugs, MINOCIN® (minocycline) for Injection should be used only to treat or prevent infections that are proven or strongly suspected to be caused by susceptible bacteria. When culture and susceptibility information are available, they should be considered in selecting or modifying antibacterial therapy. In the absence of such data, local epidemiology and susceptibility patterns may contribute to the empiric selection of therapy.

CONTRAINDICATIONS

This drug is contraindicated in persons who have shown hypersensitivity to any of the tetracyclines or to any of the components of the product formulation.

WARNINGS

Tooth Development

MINOCIN, like other tetracycline-class antibacterials, can cause fetal harm when administered to a pregnant woman. If any tetracycline is used during pregnancy, or if the patient becomes pregnant while taking these drugs, the patient should be apprised of the potential hazard to the fetus. The use of drugs of the tetracycline class during tooth development (last half of pregnancy, infancy, and childhood to the age of 8 years) may cause permanent discoloration of the teeth (yellow-gray-brown).

This adverse reaction is more common during long-term use of the drugs but has been observed following repeated short-term courses. Enamel hypoplasia has also been reported. Tetracycline drugs, therefore, should not be used during tooth development unless other drugs are not likely to be effective or are contraindicated.

Skeletal Development

All tetracyclines form a stable calcium complex in any bone-forming tissue. A decrease in the fibula growth rate has been observed in premature human infants given oral tetracycline in doses of 25 mg/kg every six hours. This reaction was shown to be reversible when the drug was discontinued.

Results of animal studies indicate that tetracyclines cross the placenta, are found in fetal tissues, and can have toxic effects on the developing fetus (often related to retardation of skeletal development). Evidence of embryotoxicity has been noted in animals treated early in pregnancy.

Dermatologic Reaction

Drug Rash with Eosinophilia and Systemic Symptoms (DRESS) including fatal cases have been reported with minocycline use. Fixed drug eruptions have occurred with minocycline and other tetracyclines. Worsening severity upon subsequent administrations, including generalized bullous fixed drug eruption, has been observed with other tetracyclines (see ADVERSE REACTIONS). If severe skin reactions occur, discontinue MINOCIN immediately and institute appropriate therapy.

Anti-anabolic Action

The anti-anabolic action of the tetracyclines may cause an increase in BUN. While this is not a problem in those with normal renal function, in patients with significantly impaired function, higher serum levels of tetracycline may lead to azotemia, hyperphosphatemia, and acidosis. Under such conditions, monitoring of creatinine and BUN is recommended, and the total daily dosage should not exceed 200 mg in 24 hours (See DOSAGE AND ADMINISTRATION). If renal impairment exists, even usual oral or parenteral doses may lead to systemic accumulation of the drug and possible liver toxicity.

Photosensitivity

Photosensitivity manifested by an exaggerated sunburn reaction has been observed in some individuals taking tetracyclines. This has been reported with minocycline.

Central Nervous System Effects

Central nervous system side effects including light-headedness, dizziness or vertigo have been reported. Patients who experience these symptoms should be cautioned about driving vehicles or using hazardous machinery while on minocycline therapy. These symptoms may disappear during therapy and usually disappear rapidly when the drug is discontinued.

Clostridium difficile associated diarrhea (CDAD) has been reported with use of nearly all antibacterial agents, including MINOCIN®, and may range in severity from mild diarrhea to fatal colitis. Treatment with antibacterial agents alters the normal flora of the colon leading to overgrowth of C. difficile.

C. difficile produces toxins A and B which contribute to the development of CDAD. Hypertoxin producing strains of C. difficile cause increased morbidity and mortality, as these infections can be refractory to antimicrobial therapy and may require colectomy. CDAD must be considered in all patients who present with diarrhea following antibacterial use. Careful medical history is necessary since CDAD has been reported to occur over two months after the administration of antibacterial agents.

If CDAD is suspected or confirmed, ongoing antibacterial use not directed against C. difficile may need to be discontinued. Appropriate fluid and electrolyte management, protein supplementation, antibacterial treatment of C. difficile, and surgical evaluation should be instituted as clinically indicated.

Intracranial Hypertension

Intracranial hypertension (IH, pseudotumor cerebri) has been associated with the use of tetracyclines including Minocin. Clinical manifestations of IH include headache, blurred vision, diplopia, and vision loss; papilledema can be found on fundoscopy. Women of childbearing age who are overweight or have a history of IH are at greater risk for developing tetracycline associated IH. Concomitant use of isotretinoin and Minocin should be avoided because isotretinoin is also known to cause pseudotumor cerebri.

Although IH typically resolves after discontinuation of treatment, the possibility for permanent visual loss exists. If visual disturbance occurs during treatment, prompt ophthalmologic evaluation is warranted. Since intracranial pressure can remain elevated for weeks after drug cessation patients should be monitored until they stabilize.

PRECAUTIONS

General

As with other antibacterial preparations, use of this drug may result in overgrowth of nonsusceptible organisms, including fungi. If superinfection occurs, the antibacterial should be discontinued and appropriate therapy instituted.

Hepatotoxicity has been reported with minocycline; therefore, minocycline should be used with caution in patients with hepatic dysfunction and in conjunction with other hepatotoxic drugs.

Incision and drainage or other surgical procedures should be performed in conjunction with antibacterial therapy when indicated.

MINOCIN® (minocycline) for Injection contains magnesium sulfate heptahydrate (See DESCRIPTION). Because magnesium is excreted primarily by the kidney, serum levels of magnesium should be monitored in patients with renal impairment (See DOSAGE AND ADMINISTRATION).

Because MINOCIN® (minocycline) for Injection contains magnesium (See DESCRIPTION), close monitoring is recommended in patients with heart block or myocardial damage.

Prescribing MINOCIN® for Injection in the absence of a proven or strongly suspected bacterial infection or a prophylactic indication is unlikely to provide benefit to the patient and increases the risk of the development of drug-resistant bacteria.

Information for Patients

Patients should be counseled that antibacterial drugs including MINOCIN® (minocycline) for Injection should only be used to treat bacterial infections. They do not treat viral infections (e.g., the common cold). When MINOCIN® (minocycline) for Injection is prescribed to treat a bacterial infection, patients should be told that although it is common to feel better early in the course of therapy, the medication should be taken exactly as directed. Skipping doses or not completing the full course of therapy may (1) decrease the effectiveness of the immediate treatment and (2) increase the likelihood that bacteria will develop resistance and will not be treatable by MINOCIN® (minocycline) for Injection or other antibacterial drugs in the future.

Diarrhea is a common problem caused by antibacterials which usually ends when the antibacterial is discontinued. Sometimes after starting treatment with antibacterial drugs, patients can develop watery and bloody stools (with or without stomach cramps and fever) even as late as two or more months after having taken the last dose of the antibacterial. If this occurs, patients should contact their physician as soon as possible.

Laboratory Tests

Periodic laboratory evaluation of organ systems, including hematopoietic, renal, and hepatic studies should be performed.

All patients with gonorrhea should have a serologic test for syphilis at the time of diagnosis. Patients treated with minocycline should have a follow-up serologic test for syphilis after 3 months.

Drug Interactions

Because tetracyclines have been shown to depress plasma prothrombin activity, patients who are on anticoagulant therapy may require downward adjustment of their anticoagulant dosage.

Since bacteriostatic drugs may interfere with the bactericidal action of penicillin, it is advisable to avoid giving tetracyclines in conjunction with penicillin.

Concurrent use of tetracyclines with oral contraceptives may render oral contraceptives less effective.

Administration of isotretinoin should be avoided shortly before, during, and shortly after minocycline therapy. Each drug alone has been associated with pseudotumor cerebri (See PRECAUTIONS).

Increased risk of ergotism when ergot alkaloids or their derivatives are given with tetracyclines.

MINOCIN® (minocycline) for Injection contains magnesium sulfate heptahydrate (See DESCRIPTION). Potentially serious drug interactions may occur when intravenous magnesium sulfate heptahydrate is given concomitantly with CNS depressants, neuromuscular blocking agents and cardiac glycosides.

Drug/Laboratory Test Interactions

False elevations of urinary catecholamine levels may occur due to interference with the fluorescence test.

Carcinogenesis, Mutagenesis, Impairment of Fertility

Dietary administration of minocycline in long-term tumorigenicity studies in rats resulted in evidence of thyroid tumor production. Minocycline has also been found to produce thyroid hyperplasia in rats and dogs. In addition, there has been evidence of oncogenic activity in rats in studies with a related antibacterial, oxytetracycline (i.e., adrenal and pituitary tumors). Likewise, although mutagenicity studies of minocycline have not been conducted, positive results in in vitro mammalian cell assays (i.e., mouse lymphoma and Chinese hamster lung cells) have been reported for related antibacterials (tetracycline hydrochloride and oxytetracycline). Segment I (fertility and general reproduction) studies have provided evidence that minocycline impairs fertility in male rats.

Pregnancy

Teratogenic Effects

(See WARNINGS)

All pregnancies have a background risk of birth defects, loss, or other adverse outcome regardless of drug exposure. There are no adequate and well-controlled studies on the use of minocycline in pregnant women. Minocycline, like other tetracycline-class antibacterials, crosses the placenta and may cause fetal harm when administered to a pregnant woman. Rare spontaneous reports of congenital anomalies including limb reduction have been reported in post-marketing experience. Only limited information is available regarding these reports; therefore, no conclusion on causal association can be established. If minocycline is used during pregnancy or if the patient becomes pregnant while taking this drug, the patient should be apprised of the potential hazard to the fetus.

Nonteratogenic Effects

(See WARNINGS)

Labor and Delivery

The effect of tetracyclines on labor and delivery is unknown.

Nursing Mothers

Tetracyclines are excreted in human milk. Because of the potential for serious adverse reactions in nursing infants from tetracyclines, a decision should be made whether to discontinue nursing or discontinue the drug, taking into account the importance of the drug to the mother. (See WARNINGS).

Pediatric Use

Minocycline is not recommended for use in children below 8 years of age unless the expected benefits of therapy outweigh the risks (See WARNINGS).

Geriatric Use

Clinical studies of intravenous minocycline did not include sufficient numbers of subjects aged 65 and over to determine whether they respond differently from younger subjects. In general, dose selection for an elderly patient should be cautious, usually starting at the low end of the dosing range, reflecting the greater frequency of decreased hepatic, renal, or cardiac function, and of concomitant disease or other drug therapy (See WARNINGS, DOSAGE AND ADMINISTRATION).

ADVERSE REACTIONS

The following adverse reactions have been observed in patients receiving tetracyclines.

Body as a whole: Fever, and discoloration of secretions.

Gastrointestinal: Anorexia, nausea, vomiting, diarrhea, dyspepsia, stomatitis, glossitis, dysphagia, enamel hypoplasia, enterocolitis, pseudomembranous colitis, pancreatitis, inflammatory lesions (with monilial overgrowth) in the oral and anogenital regions. These reactions have been caused by both the oral and parenteral administration of tetracyclines.

Genitourinary: Vulvovaginitis.

Hepatic toxicity: Hyperbilirubinemia, hepatic cholestasis, increases in liver enzymes, fatal hepatic failure, and jaundice. Hepatitis, including autoimmune hepatitis, and liver failure have been reported (See PRECAUTIONS).

Skin: Alopecia, erythema nodosum, hyperpigmentation of nails, pruritus, toxic epidermal necrolysis, and vasculitis, maculopapular and erythematous rashes. Exfoliative dermatitis has been reported. Fixed drug eruptions have been reported. Lesions occurring on the glans penis have caused balanitis. Erythema multiforme and Stevens-Johnson syndrome have been reported. Photosensitivity is discussed above (See WARNINGS). Pigmentation of the skin and mucous membranes has been reported.

Local Reactions: Injection site erythema and injection site pain.

Respiratory: Cough, dyspnea, bronchospasm, exacerbation of asthma, and pneumonitis.

Renal toxicity: Interstitial nephritis. Elevations in BUN have been reported and are apparently dose related (See WARNINGS). Acute renal failure has been reported.

Musculoskeletal: Arthralgia, arthritis, bone discoloration, myalgia, joint stiffness, and joint swelling.

Hypersensitivity reactions: Urticaria, angioneurotic edema, polyarthralgia, anaphylaxis/anaphylactoid reaction (including shock and fatalities), anaphylactoid purpura, myocarditis, pericarditis, exacerbation of systemic lupus erythematosus, and pulmonary infiltrates with eosinophilia have been reported. A lupus-like syndrome and serum sickness-like reactions also have been reported.

Blood: Agranulocytosis, hemolytic anemia, thrombocytopenia, leukopenia, neutropenia, pancytopenia, and eosinophilia have been reported.

Central Nervous System: Convulsions, dizziness, hypesthesia, paresthesia, sedation, and vertigo. Pseudotumor cerebri (benign intracranial hypertension) in adults and bulging fontanels in infants (See PRECAUTIONS - General). Headache has also been reported.

Other: Thyroid cancer has been reported in the post-marketing setting in association with minocycline products. When minocycline therapy is given over prolonged periods, monitoring for signs of thyroid cancer should be considered. When given over prolonged periods, tetracyclines have been reported to produce brown-black microscopic discoloration of the thyroid gland. Cases of abnormal thyroid function have been reported.

Tooth discoloration in pediatric patients less than 8 years of age (See WARNINGS) and in adults has been reported.

Oral cavity discoloration (including tongue, lip, and gum) have been reported.

Tinnitus and decreased hearing have been reported in patients on MINOCIN® (minocycline for injection).

The following syndromes have been reported. In some cases involving these syndromes, death has been reported. As with other serious adverse reactions, if any of these syndromes are recognized, the drug should be discontinued immediately:

Hypersensitivity syndrome consisting of cutaneous reaction (such as rash or exfoliative dermatitis), eosinophilia, and one or more of the following: hepatitis, pneumonitis, nephritis, myocarditis, and pericarditis. Fever and lymphadenopathy may be present.

Lupus-like syndrome consisting of positive antinuclear antibody; arthralgia, arthritis, joint stiffness, or joint swelling; and one or more of the following: fever, myalgia, hepatitis, rash, and vasculitis.

Serum sickness-like syndrome consisting of fever; urticaria or rash; and arthralgia, arthritis, joint stiffness, or joint swelling. Eosinophilia may be present.

MINOCIN® (minocycline) for Injection contains magnesium sulfate heptahydrate (See DESCRIPTION). Adverse effects that may be associated with magnesium intoxication include flushing, sweating, hypotension, depressed reflexes, flaccid paralysis, hypothermia, circulatory collapse, cardiac and CNS depression proceeding to respiratory paralysis (See PRECAUTIONS).

OVERDOSAGE

The adverse events more commonly seen in overdose are dizziness, nausea, and vomiting.

No specific antidote for minocycline is known.

In case of overdosage, discontinue medication, treat symptomatically, and institute supportive measures. Minocycline is not removed in significant quantities by hemodialysis or peritoneal dialysis.

DOSAGE AND ADMINISTRATION

THE USUAL DOSAGE AND FREQUENCY OF ADMINISTRATION OF MINOCYCLINE DIFFERS FROM THAT OF THE OTHER TETRACYCLINES. EXCEEDING THE RECOMMENDED DOSAGE MAY RESULT IN AN INCREASED INCIDENCE OF SIDE EFFECTS.

Note: Rapid administration is to be avoided. Parenteral therapy is indicated only when oral therapy is not adequate or tolerated. Oral therapy should be instituted as soon as possible. If intravenous therapy is given over prolonged periods of time, thrombophlebitis may result.

For Pediatric Patients above 8 years of Age

Usual pediatric dose: Initial dose of 4 mg/kg, then 2 mg/kg administered over 60 minutes every 12 hours, not to exceed the usual adult dose.

Adults

Usual adult dose: Initial dose of 200 mg, then 100 mg administered over 60 minutes every 12 hours and should not exceed 400 mg in 24 hours.

The lyophilized powder should be reconstituted with 5 mL Sterile Water for Injection USP and immediately further diluted in 100 mL to 1,000 mL with Sodium Chloride Injection USP, Dextrose Injection USP, or Dextrose and Sodium Chloride Injection USP, or in 250 mL to 1000 mL Lactated Ringer's Injection USP, but not with other solutions containing calcium because a precipitate may form especially in neutral and alkaline solutions.

When diluted in compatible solutions, the pH usually ranges from 4.5 to 6.0.

Once diluted into an intravenous bag, MINOCIN® for Injection may be stored either at room temperature for up to 4 hours or refrigerated at 2 to 8°C (36 to 46°F) for up to 24 hours. Any unused portions must be discarded after that period.

The pharmacokinetics of minocycline in patients with renal impairment (CLCR <80 mL/min) have not been fully characterized. Current data are insufficient to determine if a dosage adjustment is warranted. The total daily dosage should not exceed 200 mg in 24 hours in patients with renal impairment. However, due to the anti-anabolic effect of tetracyclines, BUN and creatinine should be monitored (See WARNINGS). Because MINOCIN (minocycline) for Injection contains magnesium sulfate heptahydrate, serum levels of magnesium should be monitored in patients with renal impairment (See DESCRIPTION, PRECAUTIONS).

Parenteral drug products should be inspected visually for particulate matter and discoloration prior to administration, whenever solution and container permit.

Incompatibilities

Additives or other medications should not be added to MINOCIN single-dose vials or infused simultaneously through the same intravenous line including Y-connectors. If the same intravenous line is used for sequential infusion of additional medications, the line should be flushed before and after infusion of MINOCIN with Sodium Chloride Injection USP, Dextrose Injection USP, Dextrose and Sodium Chloride Injection USP, or Lactated Ringer's Injection USP.

HOW SUPPLIED

MINOCIN® (minocycline) for Injection is supplied as 100 mg single-dose vials of sterile lyophilized powder.

NDC 70842-160-01: 100 mg single-dose vial
NDC 70842-160-10: units of 10 × 1 single-dose 100 mg vials

STORAGE AND HANDLING

Store at Controlled Room Temperature 20° to 25°C (68° to 77°F).

ANIMAL PHARMACOLOGY AND TOXICOLOGY

Minocycline hydrochloride has been observed to cause a dark discoloration of the thyroid in experimental animals (rats, minipigs, dogs, and monkeys). In the rat, chronic treatment with minocycline hydrochloride has resulted in goiter accompanied by elevated radioactive iodine uptake and evidence of thyroid tumor production. Minocycline hydrochloride has also been found to produce thyroid hyperplasia in rats and dogs.

This product's label may have been updated. For current package insert and further product information, please visit www.minociniv.com or call our toll-free number:1-844-633-6568. Call between 9:00 a.m. and 5:00 p.m. Eastern Time, Monday through Friday.

Manufactured for Rempex Pharmaceuticals, Inc.,
a wholly-owned subsidiary of Melinta Therapeutics, LLC
All rights reserved.

Marketed and Distributed by
Melinta Therapeutics, LLC
Parsippany, New Jersey 07054

3/2025

MEL080-R004

PRINCIPAL DISPLAY PANEL - 100 mg Vial Carton

Rx only
NDC 70842-160-10

10 Vials

Minocin®
(minocycline)
for injection

100 mg per vial

Must be reconstituted
then diluted.
For Intravenous Infusion.
Sterile Single-Dose Vials.
Discard Unused Portion.

Each vial contains minocycline hydrochloride (equivalent to
100 mg minocycline), magnesium sulfate heptahydrate and
sodium hydroxide (to adjust pH 4.5-5.0).

Usual adult dose: Initial dose of 200 mg, then 100 mg every
12 hours and should not exceed 400 mg in 24 hours.

Reconstitution: Reconstitute each vial with 5 mL of Sterile
Water for Injection.

Dilution: Reconstituted solution must be further diluted in
100 mL to 1,000 mL for infusion.

See package insert for detailed instructions for diluting,
indications and dosage.